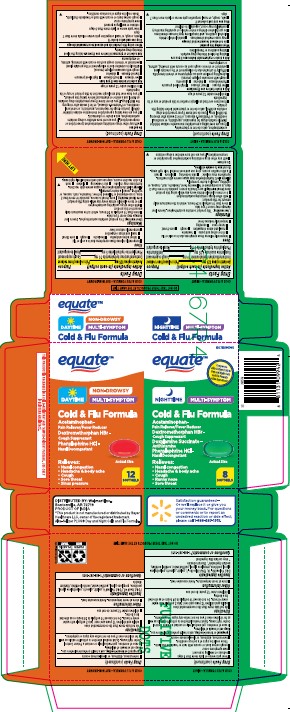 DRUG LABEL: Equate Health Non Drowsy DAY Cold and Flu Plus and NIGHTTIME Cold and Flu Plus
NDC: 79903-133 | Form: KIT | Route: ORAL
Manufacturer: Wal-Mart Stores Inc
Category: otc | Type: HUMAN OTC DRUG LABEL
Date: 20260126

ACTIVE INGREDIENTS: PHENYLEPHRINE HYDROCHLORIDE 5 mg/1 1; ACETAMINOPHEN 325 mg/1 1; DEXTROMETHORPHAN HYDROBROMIDE 10 mg/1 1; DEXTROMETHORPHAN HYDROBROMIDE 10 mg/1 1; PHENYLEPHRINE HYDROCHLORIDE 5 mg/1 1; DOXYLAMINE SUCCINATE 6.25 mg/1 1; ACETAMINOPHEN 325 mg/1 1
INACTIVE INGREDIENTS: FD&C YELLOW NO. 6; GELATIN; GLYCERIN; POLYETHYLENE GLYCOL 400; POVIDONE; PROPYLENE GLYCOL; SORBITOL; FD&C RED NO. 40; TITANIUM DIOXIDE; D&C YELLOW NO. 10; FD&C BLUE NO. 1; GELATIN; GLYCERIN; POLYETHYLENE GLYCOL 400; POVIDONE; PROPYLENE GLYCOL; SORBITOL; SORBITAN; SODIUM HYDROXIDE; TITANIUM DIOXIDE

Equate Non Drowsy DAY Cold and Flu Formula and NIGHTTIME Cold and Flu Formula

Active ingredients (in each softgel)

Equate Health COLD & FLU FORMULA DAY NON-DROWSY

Acetaminophen 325 mg
Dextromethorphan hydrobromide 10 mg
Phenylephrine hydrochloride 5 mg

Equate Health COLD & FLU FORMULA NIGHT

Acetaminophen 325 mg
Dextromethorphan hydrobromide 10 mg
Phenylephrine hydrochloride 5 mg

Purposes

DAY COLD & FLU FORMULA

Pain reliever/fever reducer

Cough suppressant

Nasal decongestant

NIGHT COLD & FLU FORMULA

Pain reliever/fever reducer

Cough suppressant

Antihistamine

Nasal decongestant

Uses

DAY COLD & FLU FORMULA

temporarily relieves these symptoms due to a cold or flu:
minor aches and pains
headache
cough
sore throat
nasal and sinus congestion
temporarily reduces fever

NIGHT COLD & FLU FORMULA

Pain reliever/fever reducer

Cough suppressant

Antihistamine

Nasal decongestant

undefined

Liver warning

DAY COLD & FLU FORMULA

These products contain acetaminophen. Severe liver damage may occur if you take

- more than 10 softgels in 24 hours, which is the maximum daily amount for this product
- with other drugs containing acetaminophen
- 3 or more alcoholic drinks every day while using this product

Sore throat warning

If sore throat is severe, persists for more than 2 days, is accompanied or followed by fever, headache, rash, nausea, or vomiting, consult a doctor promptly.

Allergy alert: Acetaminophen may cause severe skin reactions. Symptoms may include:

- skin reddening
- blisters
- rash

If a skin reaction occurs, stop use and seek medical help right away.

NIGHTTIME COLD & FLU FORMULA

Liver warning

These products contain acetaminophen. Severe liver damage may occur if you take

- more than 10 softgels in 24 hours, which is the maximum daily amount for this product
- with other drugs containing acetaminophen
- 3 or more alcoholic drinks every day while using this product

Sore throat warning

If sore throat is severe, persists for more than 2 days, is accompanied or followed by fever, headache, rash, nausea, or vomiting, consult a doctor promptly.

Allergy alert: Acetaminophen may cause severe skin reactions. Symptoms may include:

- skin reddening
- blisters
- rash

If a skin reaction occurs, stop use and seek medical help right away.

Do not use to sedate children.

Do not use

DAY COLD & FLU FORMULA

- with any other drug containing acetaminophen (prescription or nonprescription). If you are not sure whether a drug contains acetaminophen, ask a doctor or pharmacist.
- if you are now taking a prescription monoamine oxidase inhibitor (MAOI) (certain drugs for depression, psychiatric, or emotional conditions, or Parkinson's disease), or for 2 weeks after stopping the MAOI drug. If you do not know if your prescription drug contains an MAOI, ask a doctor or pharmacist before taking this product.
- if you have ever had an allergic reaction to this product or any of its ingredients
- in children under 12 years of age

NIGHTTIME COLD & FLU FORMULA

- with any other drug containing acetaminophen (prescription or nonprescription). If you are not sure whether a drug contains acetaminophen, ask a doctor or pharmacist.
- if you are now taking a prescription monoamine oxidase inhibitor (MAOI) (certain drugs for depression, psychiatric, or emotional conditions, or Parkinson's disease), or for 2 weeks after stopping the MAOI drug. If you do not know if your prescription drug contains an MAOI, ask a doctor or pharmacist before taking this product.
- if you have ever had an allergic reaction to this product or any of its ingredients
- in children under 12 years of age

Ask a doctor before use if you have

DAYTIME COLD & FLU FORMULA

- liver disease
- heart disease
- high blood pressure
- thyroid disease
- diabetes
- cough with excessive phlegm (mucus)
- difficulty in urination due to enlargement of the prostate gland
- persistent or chronic cough such as occurs with smoking, asthma, or emphysema

NIGHTTIME COLD & FLU FORMULA

- liver disease
- heart disease
- high blood pressure
- thyroid disease
- diabetes
- glaucoma
- cough with excessive phlegm (mucus)
- a breathing problem such as emphysema or chronic bronchitis
- difficulty in urination due to enlargement of the prostate gland
- persistent or chronic cough such as occurs with smoking, asthma, or emphysema

ASK DOCTOR/PHARMACIST

DAYTIME COLD & FLU FORMULA

Ask a doctor or pharmacist before use if you are taking the blood thinning drug warfarin.

NIGHTTIME COLD & FLU FORMULA

- taking the blood thinning drug warfarin
- taking sedatives or tranquilizers

When using this product

DAYTIME COLD & FLU FORMULA

When using this product do not exceed recommended dosage

NIGHTTIME COLD & FLU FORMULA

- do not exceed recommended dosage
- may cause marked drowsiness
- avoid alcoholic drinks
- alcohol, sedatives, and tranquilizers may increase drowsiness
- be careful when driving a motor vehicle or operating machinery
- excitability may occur, especially in children

Stop use and ask a doctor if

DAYTIME COLD & FLU FORMULA

- pain, cough, or nasal congestion gets worse or lasts more than 7 days
- fever gets worse or lasts more than 3 days
- redness or swelling is present
- new symptoms occur
- cough comes back or occurs with rash or headache that lasts.

These could be signs of a serious condition.

- nervousness, dizziness, or sleeplessness occurs

NIGHTTIME COLD &FLU FORMULA

- pain, cough, or nasal congestion gets worse or lasts more than 7 days
- fever gets worse or lasts more than 3 days
- redness or swelling is present
- new symptoms occur
- cough comes back or occurs with rash or headache that lasts.

These could be signs of a serious condition.

- nervousness, dizziness, or sleeplessness occurs

PREGNANCY OR BREAST FEEDING

If pregnant or breast-feeding, ask a health professional before use.

KEEP OUT OF REACH OF CHILDREN

If pregnant or breast-feeding, ask a health professional before use.

Directions

DAY COLD & FLU FORMULA

- do not take more than the recommended dose
- adults and children 12 years and over: take 2 softgels with water every 4 hours. Do not exceed 10 softgels in 24 hours or as directed by a doctor.
- children under 12 years: do not use

NIGHTTIME COLD & FLU FORMULA

- do not take more than the recommended dose
- adults and children 12 years and over: take 2 softgels with water every 4 hours. Do not exceed 10 softgels in 24 hours or as directed by a doctor.
- children under 12 years: do not use

Other information

- store at room temperature. Avoid excessive heat.

Inactive ingredients

DAY COLD & FLU FORMULA

FD&C Red# 40, FD&C Yellow# 6, gelatin, glycerin, polyethylene glycol, povidone, propylene glycol, purified water, sorbitol sorbitan, titanium dioxide

NIGHTTIME COLD & FLU FORMULA

D&C Yellow No. 10, FD&C Blue No. 1, gelatin, glycerin, polyethylene, glycol-400, povidone, propylene glycol, purified water, shellac, sorbitol
sorbitan, sodium hydroxide, titanium dioxide

Questions or comments?

1-888-287-1915

Principal Display Panel

Equate NON-DROWSY DAY Cold & Flu Formula and NIGHTTIME Cold & Flu Formula 20ct

Compare to the active ingredients in

Alka-Seltzer PLUS® Day and Night Cold and Flu Formula*

NON-DROWSY DAY

Cold & Flu Formula

ACETAMINOPHEN- Pain reliever; Fever reducer

DEXTROMETHORPHAN HBr - Cough suppressant

PHENYLEPHRINE HCI - Nasal decongestant

Relieves:

Nasal congestion; Cough;

Headache & body ache;

Sore throat; Sinus pressure

12 SOFTGELS

NIGHTTIME

Cold & Flu Formula

ACETAMINOPHEN- Pain reliever; Fever reducer

DEXTROMETHORPHAN HBr - Cough suppressant

DOXYLAMINE SUCCINATE - Antihistamine

PHENYLEPHRINE HCI - Nasal decongestant

Relieves:

Nasal congestion; Cough;

Headache & body ache;

Sore throat; Runny nose

8 SOFTGELS

THIS PRODUCT IS PACKAGED IN A CHILD-RESISTANT AND

TAMPER-EVIDENT PACKAGE. USE ONLY IF BLISTERS ARE INTACT

*This product is not manufactured or distributed by Bayer

Healthcare LLC, owner of the registered trademark

Alka-Seltzer PLUS® Day and Night Cold and Flu Formula